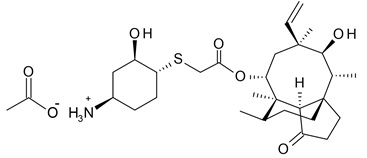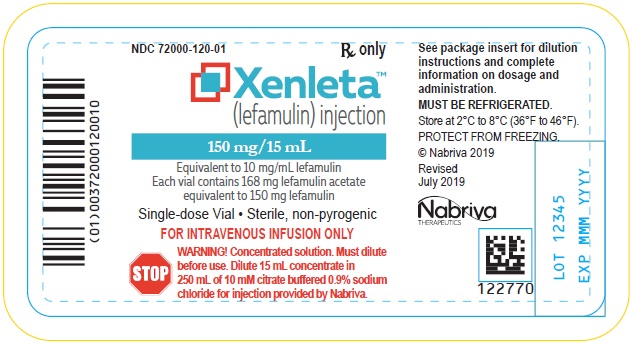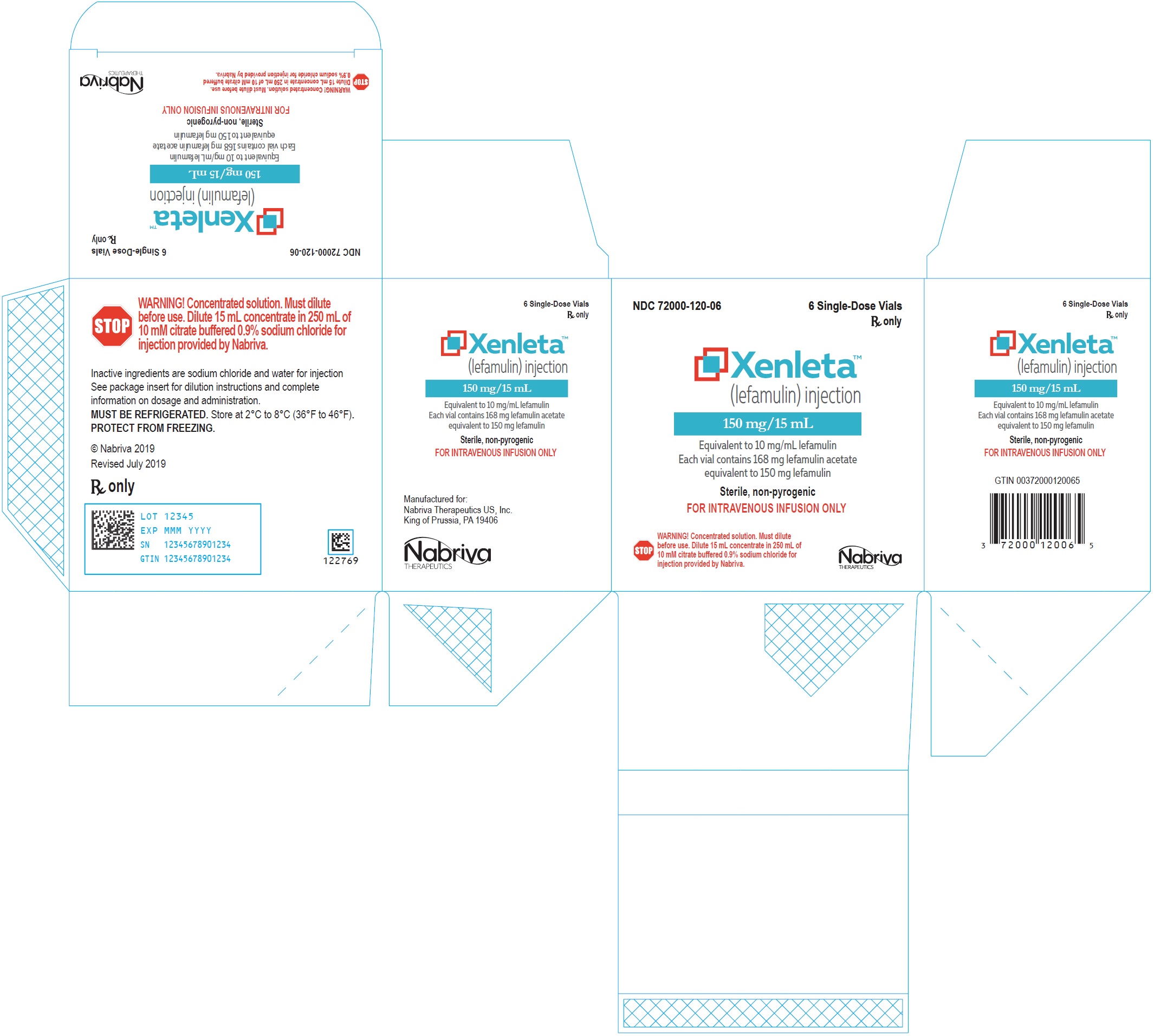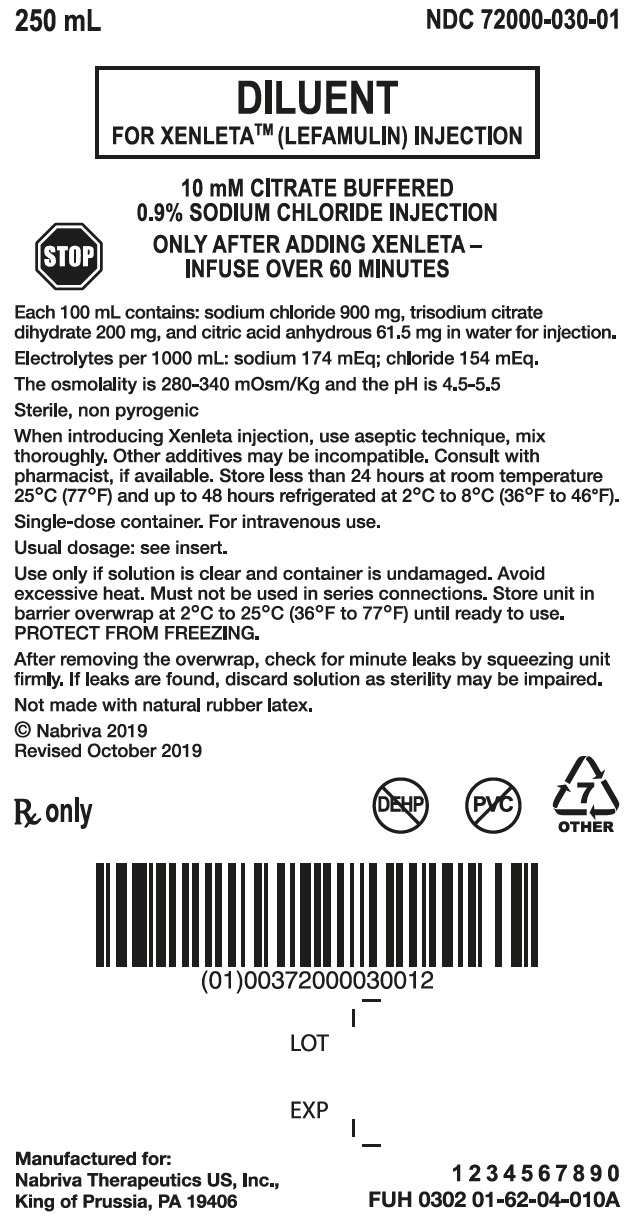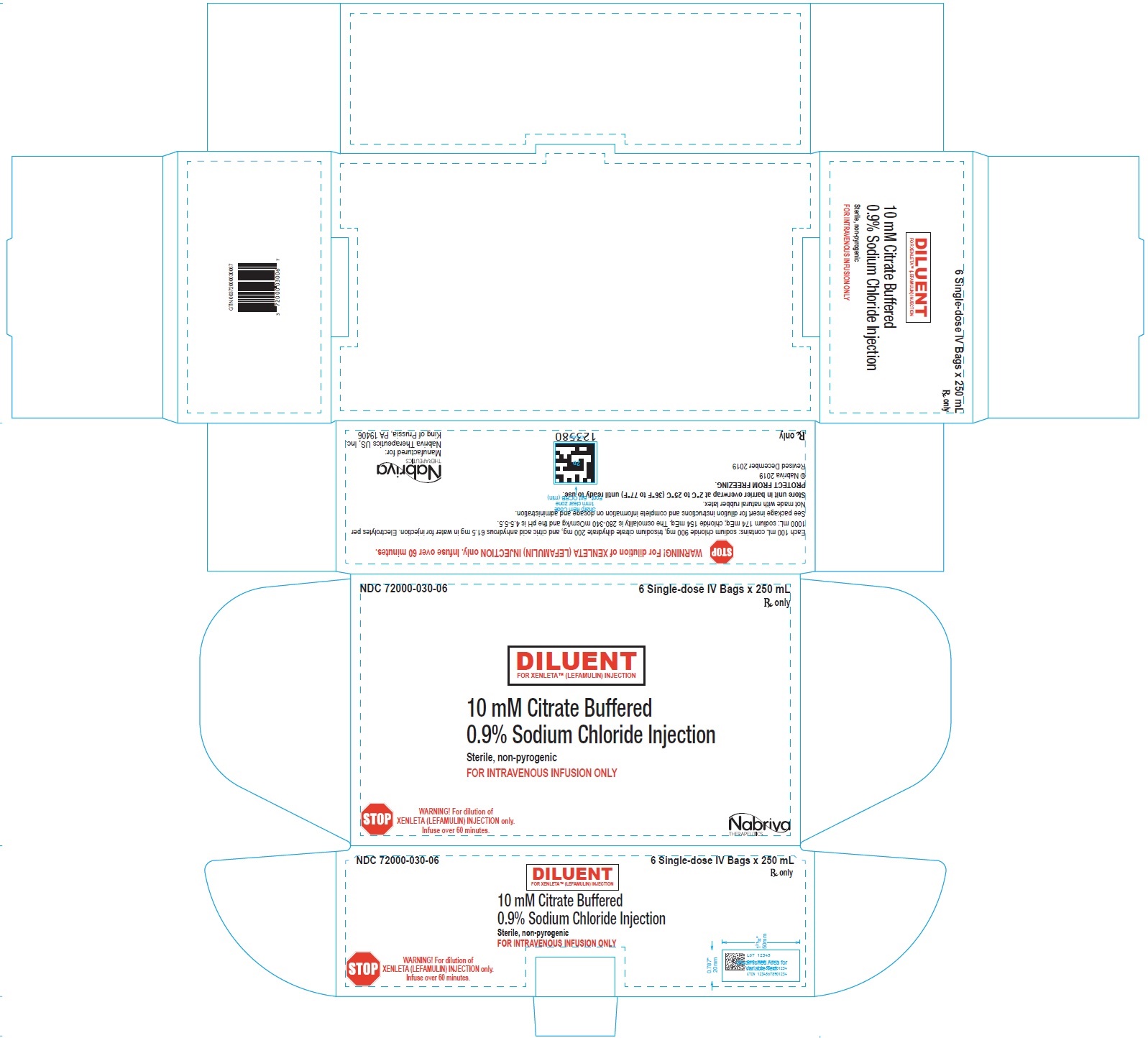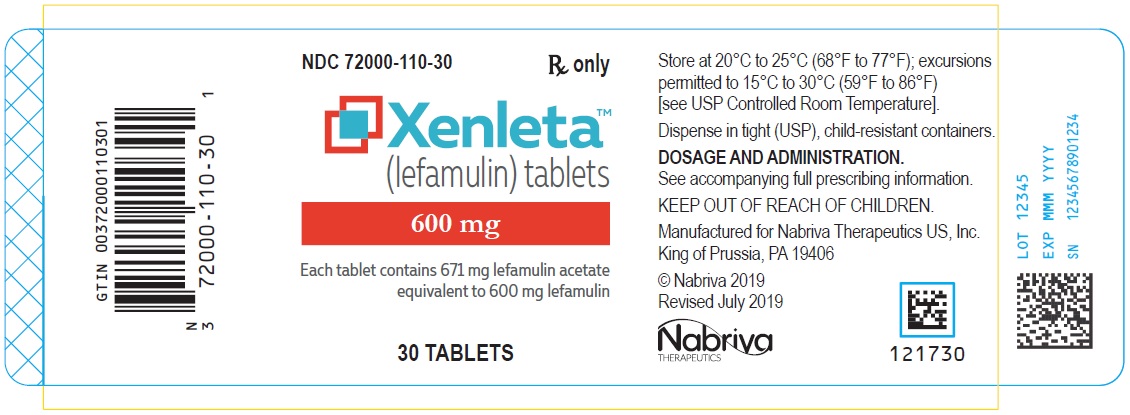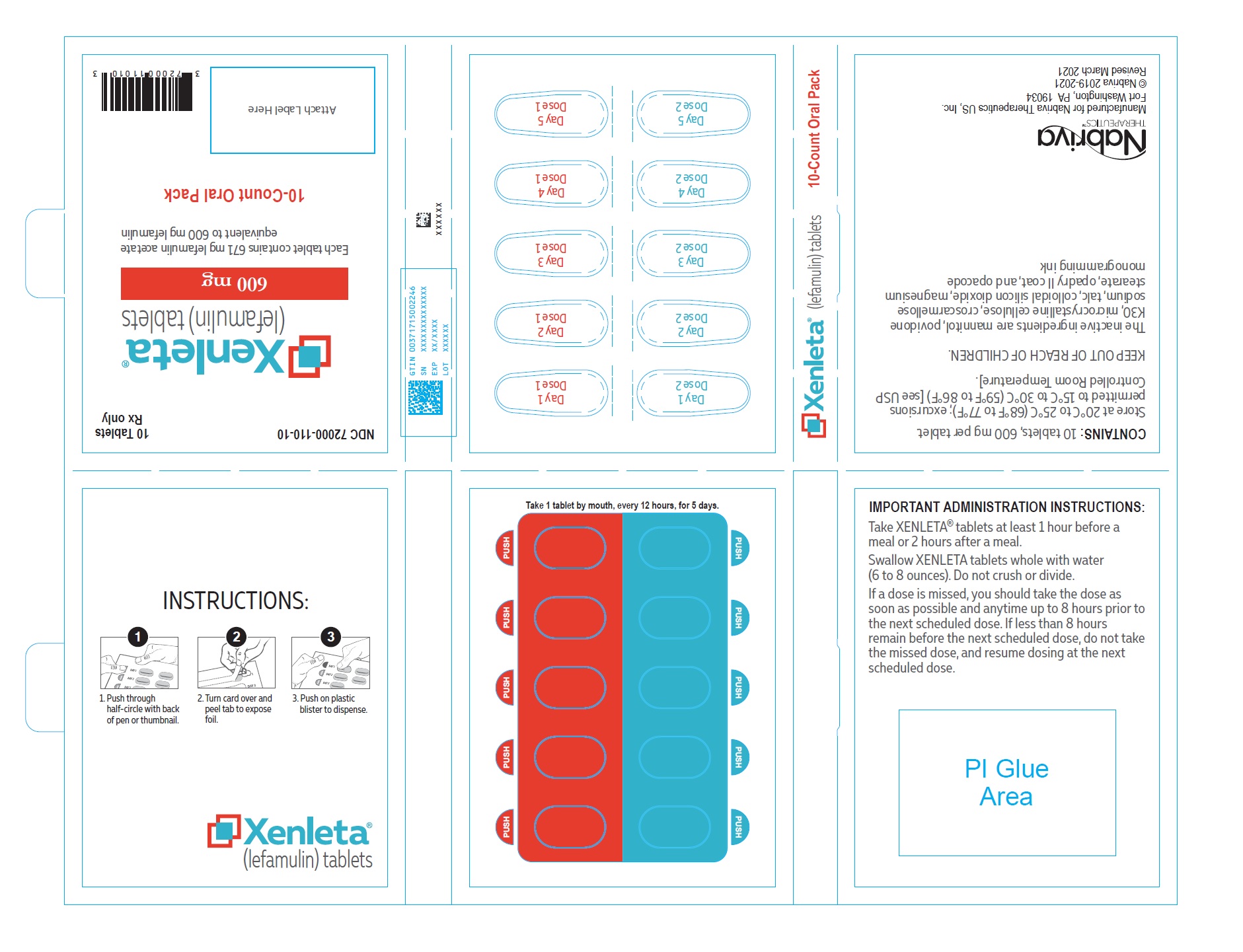 DRUG LABEL: Xenleta
NDC: 72000-120 | Form: INJECTION, SOLUTION
Manufacturer: Nabriva Therapeutics US, Inc.
Category: prescription | Type: HUMAN PRESCRIPTION DRUG LABEL
Date: 20241011

ACTIVE INGREDIENTS: LEFAMULIN ACETATE 150 mg/15 mL
INACTIVE INGREDIENTS: SODIUM CHLORIDE; WATER

HIGHLIGHTS OF PRESCRIBING INFORMATION

These highlights do not include all the information needed to use XENLETA® safely and effectively. See full prescribing information for XENLETA.
XENLETA (lefamulin) injection, for intravenous use
XENLETA (lefamulin) tablets, for oral use
Initial U.S. Approval: 2019

1 INDICATIONS AND USAGE

XENLETA is a pleuromutilin antibacterial indicated for the treatment of adults with community-acquired bacterial pneumonia (CABP) caused by susceptible microorganisms. (1.1)

To reduce the development of drug resistant bacteria and maintain the effectiveness of XENLETA and other antibacterial drugs, XENLETA should be used only to treat or prevent infections that are proven or strongly suspected to be caused by bacteria. (1.2)

2 DOSAGE AND ADMINISTRATION

- For treatment of adults with CABP, the recommended dosage of XENLETA is as follows:
  Dosage | Treatment Duration
  150 mg every 12 hours by intravenous infusion over 60 minutes* (2.1) | 5 to 7 days
  600 mg orally every 12 hours.(2.1) | 5 days
  *With the option to switch to XENLETA Tablets 600 mg every 12 hours to complete the treatment course.
- Patients with Hepatic Impairment: Reduce the dosage of XENLETA Injection to 150 mg infused over 60 minutes every 24 hours in patients with severe hepatic impairment (Child-Pugh Class C). XENLETA Tablets have not been studied in and are not recommended for patients with moderate (Child-Pugh Class B) or severe hepatic impairment (2.2).
- Administration Instruction for XENLETA Tablets: Take at least 1 hour before a meal or 2 hours after a meal. Swallow XENLETA Tablets whole with water (6 to 8 ounces). (2.3)
- Administration Instruction for XENLETA Injection: Infuse over 60 minutes. (2.3)
- See Full Prescribing Information for additional information on the administration and preparation of XENLETA Tablets and Injection. (2.4)

3 DOSAGE FORMS AND STRENGTHS

Injection

- A single-dose clear glass vial containing 150 mg of lefamulin in 15 mL of 0.9% sodium chloride for further dilution prior to intravenous infusion. (3)

Tablets

- 600 mg of lefamulin. (3)

4 CONTRAINDICATIONS

- XENLETA is contraindicated in patients with known hypersensitivity to lefamulin, pleuromutilin class drugs, or any of the components of XENLETA. (4.1)
- Concomitant use of XENLETA tablets with CYP3A substrates that prolong the QT interval is contraindicated. (4.2)

5 WARNINGS AND PRECAUTIONS

- QT Prolongation: Avoid use in patients with known QT prolongation, ventricular arrhythmias including torsades de pointes, and patients receiving drugs that prolong the QT interval such as antiarrhythmic agents. (5.1)
- Embryo-Fetal Toxicity: May cause fetal harm. Advise females of reproductive potential of the potential risk to the fetus and to use effective contraception. (5.2, 8.1, 8.3)
- Clostridioides difficile-associated Diarrhea (CDAD): Evaluate patients who develop diarrhea. (5.3)

6 ADVERSE REACTIONS

Most common adverse reactions (incidence ≥2%) are:

- XENLETA Injection: administration site reactions, hepatic enzyme elevation, nausea, hypokalemia, insomnia, headache. (6.1)
- XENLETA Tablets: diarrhea, nausea, vomiting, hepatic enzyme elevation. (6.1)

To report SUSPECTED ADVERSE REACTIONS, contact Nabriva Therapeutics US, Inc. at 1-855-5NABRIVA or FDA at 1-800-FDA-1088 or www.fda.gov/medwatch.

7 DRUG INTERACTIONS

XENLETA Injection
Strong or moderate CYP3A inducers or P-gp inducers | Avoid XENLETA unless the benefit outweighs the risk. Monitor for reduced efficacy. (7.1)
XENLETA Tablets
Strong or moderate CYP3A inducers or P-gp inducers | Avoid XENLETA unless the benefit outweighs the risk. Monitor for reduced efficacy. (7.1)
Strong CYP3A inhibitors or P-gp inhibitors | Avoid XENLETA. (7.1)
Moderate CYP3A inhibitors or P-gp inhibitors | Monitor for adverse reactions. (7.1)
CYP3A substrates that prolong the QT interval | Concomitant use is contraindicated. (4.2, 7.2)
Midazolam and other sensitive CYP3A substrates | Monitor for adverse reactions. (7.2)

8 USE IN SPECIFIC POPULATIONS

Lactation: A lactating woman should pump and discard human milk for the duration of treatment with XENLETA and for 2 days after the final dose. (8.2)

FULL PRESCRIBING INFORMATION

1 INDICATIONS AND USAGE

1.1 Community-Acquired Bacterial Pneumonia (CABP)

XENLETA is indicated for the treatment of adults with community-acquired bacterial pneumonia (CABP) caused by the following susceptible microorganisms: Streptococcus pneumoniae, Staphylococcus aureus (methicillin-susceptible isolates), Haemophilus influenzae, Legionella pneumophila, Mycoplasma pneumoniae, and Chlamydophila pneumoniae.

1.2 Usage

To reduce the development of drug-resistant bacteria and maintain the effectiveness of XENLETA and other antibacterial drugs, XENLETA should be used only to treat or prevent infections that are proven or strongly suspected to be caused by susceptible bacteria. When culture and susceptibility information are available, they should be considered in selecting or modifying antibacterial therapy. In the absence of such data, local epidemiology and susceptibility patterns may contribute to the empiric selection of therapy.

2 DOSAGE AND ADMINISTRATION

2.1 Recommended Dosage

For treatment of adults with CABP, the recommended dosage of XENLETA is described in Table 1 below. For patients with severe hepatic impairment, dosage adjustment is required [see Dosage and Administration (2.2)].

Table 1: Dosage of XENLETA in Adult CABP Patients
Dosage | Treatment Duration
150 mg every 12 hours by intravenous infusion over 60 minutes* | 5 to 7 days
600 mg orally every 12 hours | 5 days
*With the option to switch to XENLETA Tablets 600 mg every 12 hours to complete the treatment course.

2.2 Dosage Adjustment for Patients with Hepatic Impairment

Monitor patients with hepatic impairment for adverse reactions associated with XENLETA Injection and Tablets throughout the treatment period [see Use in Specific Populations (8.6) and Clinical Pharmacology (12.3)].

XENLETA Injection

Reduce the dosage of XENLETA Injection to 150 mg infused intravenously over 60 minutes every 24 hours for patients with severe hepatic impairment (Child-Pugh Class C). No dosage adjustment of XENLETA Injection is needed for patients with mild (Child-Pugh Class A) or moderate (Child-Pugh Class B) hepatic impairment.

XENLETA Tablets

XENLETA Tablets have not been studied in and are not recommended for patients with moderate (Child-Pugh Class B) or severe (Child-Pugh Class C) hepatic impairment. No dosage adjustment of XENLETA Tablets is needed for patients with mild hepatic impairment (Child-Pugh Class A).

2.3 Important Administration Instructions

XENLETA Injection

Administer XENLETA Injection by intravenous infusion over 60 minutes. Must dilute in a 250 mL solution of 10 mM citrate buffered 0.9% sodium chloride for injection supplied with XENLETA Injection before use [see Dosage and Administration (2.4)].

XENLETA Tablets

Take XENLETA Tablets at least 1 hour before a meal or 2 hours after a meal. Swallow XENLETA Tablets whole with water (6 to 8 ounces). Do not crush or divide XENLETA Tablets [see Clinical Pharmacology (12.3)].

Missed Dose

If a dose is missed, the patient should take the dose as soon as possible and anytime up to 8 hours prior to the next scheduled dose. If less than 8 hours remain before the next scheduled dose, do not take the missed dose, and resume dosing at the next scheduled dose.

2.4 Preparation of XENLETA Injection for Intravenous Infusion

- Dilute the entire 15 mL vial of XENLETA Injection into the diluent bag supplied with XENLETA injection that contains 250 mL of 10 mM citrate buffered 0.9% sodium chloride.
- Use aseptic technique when adding XENLETA Injection into the diluent bag. Mix thoroughly.
- Parenteral drug products should be inspected visually for particulate matter and discoloration prior to administration, whenever solution and container permit. Use the diluent bag only if the solution is clear and the container is undamaged.
- Do not use the diluent bag in series connections.
- Do not add other additives to the diluent bag because their compatibilities with XENLETA Injection have not been established.

2.5 Storage of XENLETA Injection After Dilution

After dilution, XENLETA Injection can be stored for up to 24 hours at room temperature and up to 48 hours when refrigerated at 2°C to 8°C (36°F to 46°F).

3 DOSAGE FORMS AND STRENGTHS

XENLETA Injection

Clear, colorless solution in a single-dose clear glass vial. Each vial contains 150 mg of lefamulin in 15 mL of 0.9% sodium chloride for further dilution [see Dosage and Administration (2.4)].

XENLETA Tablets

Blue, oval, film-coated tablet with ‘LEF 600’ printed in black on one side. Each tablet contains 600 mg of lefamulin.

4 CONTRAINDICATIONS

4.1 Hypersensitivity

XENLETA is contraindicated in patients with known hypersensitivity to lefamulin, pleuromutilin class drugs, or any of the components of XENLETA.

4.2 CYP3A4 Substrates That Prolong the QT Interval

XENLETA Tablets are contraindicated with sensitive CYP3A4 substrates that prolong the QT interval (for example, pimozide). Concomitant administration of oral XENLETA with sensitive CYP3A4 substrates may result in increased plasma concentrations of these drugs, leading to QT prolongation and cases of torsades de pointes [see Warnings and Precautions (5.1), Drug Interactions (7.2), and Clinical Pharmacology (12.3)].

5 WARNINGS AND PRECAUTIONS

5.1 QT Prolongation

XENLETA has the potential to prolong the QT interval of the electrocardiogram (ECG) in some patients. Avoid XENLETA use in the following patients:

- Patients with known prolongation of the QT interval
- Patients with ventricular arrhythmias including torsades de pointes
- Patients receiving Class IA (for example, quinidine, procainamide) or Class III (for example, amiodarone, sotalol) antiarrhythmic agents
- Patients receiving other drugs that prolong the QT interval, such as antipsychotics, erythromycin, pimozide, moxifloxacin, and tricyclic antidepressants

In patients with renal failure who require dialysis, metabolic disturbances associated with renal failure may lead to QT prolongation.

In patients with mild, moderate, or severe hepatic impairment, metabolic disturbances associated with hepatic impairment may lead to QT prolongation.

If use with XENLETA cannot be avoided in specific populations predisposed to QT prolongation or those receiving another drug that prolongs the QT interval, ECG monitoring is recommended during treatment.

The magnitude of QT prolongation may increase with increasing concentrations of XENLETA or increasing the rate of infusion of the intravenous formulation. Therefore, the recommended dose and infusion rate should not be exceeded.

5.2 Embryo-Fetal Toxicity

Based on findings from animal studies, lefamulin may cause fetal harm when administered to pregnant women. Animal studies indicate that administration of lefamulin resulted in an increased incidence of post-implantation fetal loss and stillbirths in rats and rabbits treated during the period of organogenesis or in rats treated from the beginning of organogenesis through the time of weaning. Additional rat pup deaths were observed during early lactation that were likely related to maternal treatment with lefamulin. Decreased fetal body weights and ossification in rats and rabbits, and apparent delay in sexual maturation in rats may indicate treatment-related developmental delay, while other findings such as malformations in rats at systemic exposures lower than the systemic exposure in CABP patients may indicate a risk for embryo-fetal toxicity.

Verify pregnancy status in females of reproductive potential prior to initiating XENLETA. Advise females of reproductive potential to use effective contraception during treatment with XENLETA and for 2 days after the final dose. Advise pregnant women and females of reproductive potential of the potential risk to a fetus [see Use in Specific Populations (8.1, 8.3)].

5.3 Clostridioides difficile-associated Diarrhea

Clostridioides difficile-associated diarrhea (CDAD) has been reported with use of nearly all antibacterial agents, including XENLETA, and may range in severity from mild diarrhea to fatal colitis. Treatment with antibacterial agents alters the normal flora of the colon leading to overgrowth of C. difficile.

C. difficile produces toxins A and B which contribute to the development of CDAD. Hypertoxin-producing isolates of C. difficile cause increased morbidity and mortality, as these infections can be refractory to antimicrobial therapy and may require colectomy. CDAD must be considered in all patients who present with diarrhea following antibacterial drug use. Careful medical history is necessary since CDAD has been reported to occur over two months after the administration of antibacterial agents.

If CDAD is suspected or confirmed, ongoing antibacterial drug use not directed against C. difficile may need to be discontinued. Appropriate fluid and electrolyte management, protein supplementation, antibacterial drug treatment of C. difficile, and surgical evaluation should be instituted as clinically indicated.

5.4 Development of Drug-Resistant Bacteria

Prescribing XENLETA in the absence of a proven or strongly suspected bacterial infection or a prophylactic indication is unlikely to provide benefit to the patient and increases the risk of the development of drug-resistant bacteria.

6 ADVERSE REACTIONS

The following clinically significant adverse reactions are described elsewhere in the labeling:

- QT Prolongation [see Warnings and Precautions (5.1)].
- Clostridioides difficile-associated Diarrhea [see Warnings and Precautions (5.3)].

6.1 Clinical Trials Experience

Because clinical trials are conducted under widely varying conditions, adverse reaction rates observed in the clinical trials of a drug cannot be directly compared to rates in the clinical trials of another drug and may not reflect the rates observed in practice.

XENLETA was evaluated in two clinical trials in CABP patients (Trial 1 and Trial 2). Across the two trials, a total of 641 patients were treated with XENLETA. Trial 1 (intravenous [IV] to oral dosing switch trial) enrolled 551 adult patients, 276 randomized to XENLETA (273 received at least one dose of XENLETA) and 275 randomized to moxifloxacin (273 received at least one dose of moxifloxacin). Trial 2 (oral dosing only trial) enrolled 738 adult patients, 370 randomized to XENLETA (368 received at least one dose of XENLETA) and 368 randomized to moxifloxacin (all 368 received at least one dose of moxifloxacin).

Trial 1 enrolled patients with Pneumonia Outcomes Research Team (PORT) Risk Class III-V. The mean duration of intravenous treatment was 6 days; the mean total duration of treatment was 7 days. Trial 2 enrolled patients with PORT Risk Class II-IV. The mean duration of treatment was 5 days for XENLETA and 7 days for moxifloxacin.

In Trial 1 and Trial 2 (pooled), the median age of patients treated with XENLETA was 61 (range 19-97) years; 42% of patients were 65 years or older and 18% were 75 years or older. Patients were predominantly male (58%) and white (79%) and had a median body mass index (BMI) of 26.0 (range 13.0-56.8) kg/m^2. Approximately 52% of XENLETA-treated patients had creatinine clearance (CrCl) <90 mL/min.

Serious Adverse Reactions and Adverse Reactions Leading to Discontinuation

In Trial 1 and Trial 2 (pooled), serious adverse reactions occurred in 36/641 (5.6%) patients treated with XENLETA and 31/641 (4.8%) patients treated with moxifloxacin. Treatment was discontinued due to an adverse reaction in 21/641 (3.3%) patients treated with XENLETA and 21/641 (3.3%) patients treated with moxifloxacin. Death within 28 days occurred in 8/641 (1.2%) patients treated with XENLETA and 7/641 (1.1%) patients treated with moxifloxacin.

Most Common Adverse Reactions

Table 2 and Table 3 include adverse reactions occurring in ≥2% of patients receiving XENLETA in Trials 1 and 2.

Table 2: Adverse Reactions Occurring in ≥2% of Patients Receiving XENLETA in Trial 1
Adverse Reaction | Trial 1 IV ± Oral Dosing
Adverse Reaction | XENLETA N=273 | Moxifloxacin N=273
Administration site reactions* | 7% | 3%
Hepatic enzyme elevation** | 3% | 3%
Nausea | 3% | 2%
Hypokalemia | 3% | 2%
Insomnia | 3% | 2%
Headache | 2% | 2%
*Administration site reactions include infusion site pain, infusion site phlebitis, and injection site reaction.
**Hepatic enzyme elevation includes alanine aminotransferase increased, aspartate aminotransferase increased, and liver function test increased.

Table 3: Adverse Reactions Occurring in ≥2% of Patients Receiving XENLETA in Trial 2
Adverse Reaction | Trial 2 Oral Dosing
Adverse Reaction | XENLETA N=368 | Moxifloxacin N=368
Diarrhea | 12% | 1%
Nausea | 5% | 2%
Vomiting | 3% | 1%
Hepatic enzyme elevation** | 2% | 2%
**Hepatic enzyme elevation includes alanine aminotransferase increased, aspartate aminotransferase increased, and liver function test increased.

Selected Adverse Reactions Occurring in Less Than 2% of Patients Receiving XENLETA in Trials 1 and 2

Blood and Lymphatic System Disorders: anemia, thrombocytopenia

Cardiac Disorders: atrial fibrillation, palpitations

Gastrointestinal Disorders: abdominal pain, constipation, dyspepsia, epigastric discomfort, erosive gastritis

Infections and Infestations: Clostridioides difficile colitis, oropharyngeal candidiasis, vulvovaginal candidiasis

Investigations: alkaline phosphatase increased, creatine phosphokinase increased, electrocardiogram QT prolonged, gamma-glutamyl transferase increased

Nervous System Disorders: somnolence

Psychiatric Disorders: anxiety

Renal and Urinary Disorders: urinary retention

7 DRUG INTERACTIONS

7.1 Effect of Other Drugs on XENLETA

Strong and Moderate CYP3A Inducers or P-gp Inducers

Concomitant use of oral or intravenous XENLETA with strong CYP3A4 inducers or P-gp inducers decreases lefamulin AUC and Cmax [see Clinical Pharmacology (12.3)] ,which may reduce the efficacy of XENLETA. Avoid concomitant use of XENLETA Injection and XENLETA Tablets with strong and moderate CYP3A4 inducers or P-gp inducers unless the benefit outweighs the risks.

Strong and Moderate CYP3A Inhibitors or P-gp Inhibitors

Concomitant use of XENLETA Tablets with strong CYP3A inhibitors or P-gp inhibitors increases lefamulin AUC [see Clinical Pharmacology (12.3)] , which may increase the risk of adverse reactions with XENLETA Tablets. Avoid concomitant use of XENLETA Tablets with strong CYP3A inhibitors or P-gp inhibitors. Monitor for adverse effects of XENLETA Tablets when administered concomitantly with moderate CYP3A inhibitors or P-gp inhibitors.

7.2 Effect of XENLETA on Other Drugs

CYP3A4 Substrates

Concomitant use of XENLETA Tablets with sensitive CYP3A4 substrates increases the AUC and Cmax of CYP3A4 substrates [see Clinical Pharmacology (12.3)] , which may increase the risk of toxicities associated with cardiac conduction. Concomitant use with CYP3A substrates known to prolong the QT interval is contraindicated [see Contraindications (4.2)]. Concomitant use of sensitive CYP3A substrates with XENLETA Tablets requires close monitoring for adverse effects of these drugs (for example, alprazolam, diltiazem, verapamil, simvastatin, vardenafil). Concomitant use of XENLETA Injection with CYP3A4 substrates does not affect the exposure of CYP3A4 substrates.

7.3 Drugs that Prolong QT

The pharmacodynamic interaction potential to prolong the QT interval of the electrocardiogram between XENLETA and other drugs that effect cardiac conduction is unknown. Therefore, avoid concomitant use of XENLETA Injection and XENLETA Tablets with such drugs (for example, Class IA and III antiarrhythmics, antipsychotics, erythromycin, moxifloxacin, tricyclic antidepressants).

8 USE IN SPECIFIC POPULATIONS

8.1 Pregnancy

Risk Summary

Based on findings from animal studies, lefamulin may cause fetal harm when administered to pregnant women. There are no available data on the use of XENLETA in pregnant women to evaluate for a drug-associated risk of major birth defects, miscarriage or adverse maternal or fetal outcomes.

Animal studies indicate that intravenous administration of lefamulin during organogenesis resulted in an increased incidence of prenatal mortality at mean maternal exposures 0.9 times the mean exposure in clinical patients (based on AUC0-24h), decreased fetal body weights, apparent delay in sexual maturation that suggest treatment-related developmental delay, and malformations in rats at maternal exposures greater than 0.4 times the mean exposure in CABP patients for which the litter incidence was nonexistent in concurrent controls and rare (0 to approximately 0.3%) in historical controls. Decreased ossification was seen in fetuses at all doses in a dose-related manner, suggestive of developmental delay (see Data).

The estimated background risk of major birth defects and miscarriage for the indicated population is unknown. All pregnancies have a background risk of birth defect, loss, or other adverse outcomes. In the U.S. general population, the estimated background risk of major birth defects and miscarriage in clinically recognized pregnancies is 2 to 4% and 15 to 20%, respectively.

There is a pregnancy pharmacovigilance program for XENLETA. If XENLETA is inadvertently administered during pregnancy or if a patient becomes pregnant while receiving XENLETA, healthcare providers should report XENLETA exposure by calling 1-855-5NABRIVA to enroll.

Data

Animal Data

In a prenatal and postnatal development study in rats treated from the beginning of organogenesis through lactation (Gestation Day [GD] 6 through lactation day 21), the percent of live births was reduced (87.4% compared with the concurrent control of 98.7%) in the high dose group of 100 mg/kg/day (0.9 times the mean exposure in CABP patients treated IV). Equivocal findings in that study were indicative of early post-natal mortality and apparent developmental delay that may be related to pre-natal effects.

In the rat embryo-fetal development study of IV lefamulin during organogenesis (GD 6-17), findings included late resorptions in the high-dose group and malformations (cleft palate/jaw/vertebral malformations at the mid and high doses and enlarged ventricular heart chamber with a thin ventricular wall at the high dose) for which the litter incidence was nonexistent in concurrent controls and rare in historical controls (0 to approximately 0.3%). Decreased or no ossification in a number of skeletal elements in all treated groups may indicate treatment-related developmental delay at all doses. The mean exposure at the lowest dose was approximately 0.4 times the mean exposure in CABP patients treated IV. The main human metabolite, 2R-hydroxy lefamulin, was evaluated in an embryo-fetal development study in rats after IV administration and was also associated with the same cardiac malformation seen in the above study, enlarged ventricular heart chamber with or without a thin ventricular wall (which could be associated with undetected valve or great vessel anomalies).

In the rabbit embryo-fetal development study of IV lefamulin during organogenesis (GD 6-18), low numbers of live fetuses in utero in treated groups limited evaluation of the study. Additional findings at the high dose included decreased fetal weight and decreased or no ossification of skeletal elements, which may be indicative of developmental delay. A NOAEL was not determined. The lowest dose (not fully evaluated due to fetal mortality) would correspond to a mean exposure approximately 0.1 times the mean exposure in CABP patients.

Results of animal studies indicate that lefamulin crosses the placenta and is found in fetal tissues. Following a single intravenous administration of 30 mg/kg radio-labelled lefamulin to pregnant female rats on Day 17 of gestation, radioactivity was visible in fetal tissue, with greatest concentrations measured in the placenta and fetal liver (34.3 and 8.26 mcg equivalents/g, respectively) compared to 96.6 mcg equivalents/g in the maternal liver. Radioactivity in fetal tissues generally declined rapidly, and radioactivity associated with the fetus itself was below the limit of quantification by 12 hours post-dose. Radioactivity in the placenta declined rapidly and was below the limit of quantification by 24 hours after dosing. Concentrations of radioactivity in the amniotic sac remained measurable at the final sampling time (72 hours), peaking at 6 hours post-dose. The amniotic fluid did not contain radioactivity at any time after dose administration.

8.2 Lactation

Risk Summary

There are no data on the presence of XENLETA in human milk, its effects on the breastfed infant, or its effects on milk production. Animal studies indicate that lefamulin was concentrated in the milk of lactating rats (see Data). When a drug is present in animal milk, it is likely that the drug will be present in human milk. Because of the potential for serious adverse reactions, including QT prolongation, a woman should pump and discard human milk for the duration of treatment with XENLETA and for 2 days after the final dose.

Data

Administration of a single intravenous dose of 30 mg/kg radio-labelled lefamulin to lactating rats resulted in maximal mean concentrations of radioactivity in plasma and milk at 0.25-hour post-dose (3.29 and 10.7 mcg equivalents/g, respectively) that were markedly reduced at 24 hours post-dose (0.00663 and 0.0700 mcg equivalents/g, respectively). Milk/plasma ratios increased from 3.27 at 0.25-hour post-dose to 8.33 at 6 hours post-dose. These data indicate that pups would be exposed to lefamulin and its metabolites in maternal milk.

8.3 Females and Males of Reproductive Potential

Pregnancy Testing

Verify pregnancy status in females of reproductive potential.

Contraception

Females

Advise females of reproductive potential to use effective contraception during treatment with XENLETA and for 2 days after the final dose. XENLETA may cause fetal harm when administered to a pregnant woman [see Use in Specific Populations (8.1)].

8.4 Pediatric Use

The safety and effectiveness of XENLETA in patients less than 18 years of age has not yet been established.

8.5 Geriatric Use

Of the 646 patients randomized to XENLETA in Trials 1 and 2, 268 (41.5%) were ≥65 years of age. Early clinical response (ECR) rates in the subgroup of patients ≥65 were similar to ECR rates in subjects <65 years of age and comparable across treatment groups (XENLETA versus moxifloxacin).

The adverse reaction profiles in patients ≥65 years and in patients <65 years of age were similar. The percentage of patients in the XENLETA group who had at least one adverse reaction was 30% in patients ≥65 years and 38% in patients <65 years.

8.6 Hepatic Impairment

XENLETA Injection

Dosage of XENLETA Injection should be reduced by extending the dosing interval for patients with severe hepatic impairment (Child-Pugh Class C). No dosage adjustment of XENLETA Injection is needed for patients with mild (Child-Pugh Class A) or moderate (Child-Pugh Class B) hepatic impairment.

XENLETA Tablets:

XENLETA Tablets have not been studied in patients with hepatic impairment. It is not recommended to use XENLETA Tablets for patients with moderate or severe hepatic impairment [see Dosage and Administration (2.2) and Clinical Pharmacology (12.3)].

8.7 Renal Impairment

No dosage adjustment of XENLETA is warranted in patients with renal impairment, including those on hemodialysis.

10 OVERDOSAGE

Treatment of overdose with XENLETA should consist of observation and general support measures. Lefamulin and its primary metabolite are not dialyzable.

11 DESCRIPTION

XENLETA is a semi-synthetic antibacterial agent for oral and intravenous administration.

XENLETA, a pleuromutilin derivative, is available as 14-O-{[(1R,2R,4R)-4-amino-2-hydroxy-cyclohexylsulfanyl]-acetyl}-mutilin in the form of an acetic acid salt (acetate). It is a chemical substance with a molecular weight of 567.79 grams per mole. Its empirical formula is C30H49NO7S and its chemical structure is:

XENLETA Tablets for oral administration are available as blue, oval, film-coated tablets containing 671 mg lefamulin acetate equivalent to 600 mg lefamulin. The inactive ingredients are colloidal silicon dioxide, croscarmellose sodium, FD&C Blue No 2 aluminum lake, ferrosoferric oxide, magnesium stearate, mannitol, microcrystalline cellulose, polyethylene glycol, polyvinyl alcohol (partially hydrolyzed), povidone K30, shellac glaze, talc, and titanium dioxide.

XENLETA Injection supplied as a sterile injection for intravenous use is available as a clear colorless solution in a glass vial containing 168 mg of lefamulin acetate equivalent to 150 mg of lefamulin in 15 mL of 0.9% sodium chloride. This is equivalent to 10 mg/mL lefamulin. The inactive ingredients are sodium chloride and water for injection.

XENLETA Injection must be diluted with the diluent supplied with XENLETA Injection, before administration by intravenous infusion. Each supplied diluent infusion bag contains 250 mL of 10 mM citrate buffered (pH 5) 0.9% sodium chloride. The diluent is a clear, colorless solution. The inactive ingredients are citric acid anhydrous, sodium chloride, trisodium citrate dihydrate, and water for injection. Each 100 mL contains: sodium chloride 900 mg, trisodium citrate dihydrate 200 mg, and citric acid anhydrous 61.5 mg in water for injection. Electrolytes per 1000 mL: sodium 174 mEq; chloride 154 mEq. The osmolality is 280-340 mOsm/kg and the pH is 4.5-5.5.

12 CLINICAL PHARMACOLOGY

12.1 Mechanism of Action

XENLETA is an antibacterial drug [see Microbiology (12.4)].

12.2 Pharmacodynamics

The 24 h free-drug AUC to minimal inhibitory concentration (MIC) ratio has been shown to be the best Pharmacokinetic-Pharmacodynamic (PK-PD) index for the antibacterial activity of lefamulin in animal infection models of Streptococcus pneumoniae and Staphylococcus aureus pneumonia.

Cardiac Electrophysiology

The QTcF interval prolongation risk of XENLETA was evaluated using 2 randomized, double-blind, double-dummy, active controlled (moxifloxacin 400 mg once daily), parallel group, trials (Trials 1 and 2) in adult patients with CABP. A concentration dependent QTc prolongation effect of XENLETA was observed. The mean change from baseline QTcF (90% two-sided upper confidence interval) values around Tmax on day 3 or 4 were 13.6 ms (15.5 ms) for 150 mg injection administered twice daily as infusion and 9.3 ms (10.9 ms) for 600 mg tablet administered twice daily. The mean change from baseline QTcF (90% two-sided upper confidence interval) values around Tmax for the moxifloxacin randomized comparison arm on day 3 or 4 were 16.4 ms (18.3 ms) for 400 mg injection administered once daily as infusion and 11.6 ms (13.2 ms) for 400 mg tablet administered once daily.

12.3 Pharmacokinetics

Following single-dose intravenous administration, the AUC of lefamulin increased approximately dose-proportionally while the Cmax of lefamulin increased less than dose-proportionally over a dose range of 25 mg (0.17 times the approved dose) to 400 mg (2.67 times the approved dose). Following single-dose oral administration, the AUC of lefamulin increased more than dose proportionally over a dose range of 500 mg (0.8 times the approved dose) to 750 mg (1.25 times the approved dose).

Pharmacokinetic (PK) parameters of lefamulin following administration of XENLETA Injection or Tablets to patients with CABP are listed in Table 4.

The mean lefamulin AUC0-24h and Cmax in patients with CABP were 73% and 30% higher, respectively, compared with healthy subjects.

Table 4: Pharmacokinetic (PK) Parameters of Lefamulin Following Single or Multiple Dose (Every 12 Hours) XENLETA Administered as 150 mg (Infused Over 60 Minutes) Intravenously (IV) or 600 mg Orally in Patients with CABP a
PK Parameters b | Administration Route | Arithmetic Mean (% CV)
PK Parameters b | Administration Route | Day 1 | Steady State
Cmax (mcg/mL) | IV | 3.50 (11.7) | 3.60 (14.6)
Cmax (mcg/mL) | Oral c | 2.24 (36.4) | 2.24 (37.1)
Cmin (mcg/mL) | IV | 0.398 (68.1) | 0.573 (89.4)
Cmin (mcg/mL) | Oral c | 0.593 (67.3) | 0.765 (75.7)
AUC0-24h (mcg·h/mL) | IV | 27.0 (31.8) | 28.6 (46.9)
AUC0-24h (mcg·h/mL) | Oral c | 30.7 (45.0) | 32.7 (49.2)
a Based on population PK modeling (Trial 1 for IV administration and Trial 2 for oral administration)
b Cmax=maximum plasma concentration; Cmin=trough plasma concentration; AUC0–24h=area under the plasma concentration-time curve from time zero to 24 hours
c Dose administered under fasting conditions (1 hour before or 2 hours after a meal)

Absorption

The mean oral bioavailability of XENLETA Tablets is approximately 25% and peak lefamulin plasma concentration occurred 0.88 to 2 hours after administration to healthy subjects.

Effect of Food

The concomitant administration of a single oral dose of 600 mg XENLETA Tablets with a high fat (approximately 50% of total calories from fat), high calorie breakfast (approximately 800-1000 calories) slightly reduced bioavailability. The mean relative reduction for oral XENLETA (fasted vs. fed) was on average 22.9% [90% CI: 12.2; 32.3] for the Cmax and 18.43% [90% CI: 11.7; 24.7] for the AUC0-inf.

Distribution

Mean plasma protein binding of lefamulin ranges from 94.8% at 2.35 mcg/mL to 97.1% at 0.25 mcg/mL in healthy adults.

The mean (min to max) steady state volume of distribution of lefamulin is 86.1 L (34.2 to 153 L) in patients with CABP after administration of XENLETA Injection.

Following a single IV administration of lefamulin 150 mg to healthy subjects, the highest lefamulin epithelial lining fluid (ELF) concentrations were observed at the end of infusion. The mean ELF and plasma AUC0-8 was 3.87 mcg·h/mL and 5.27 mcg·h/mL, respectively. The estimated ratio of ELF AUC to unbound plasma AUC is approximately 15.

Elimination

The mean (min to max) total body clearance of lefamulin is 11.9 L/h (2.94 to 30.0 L/h) in patients with CABP after XENLETA Injection administration.

The mean (min to max) elimination half-life of lefamulin is approximately 8 hours (3 to 20 h) in patients with CABP.

Metabolism

Lefamulin is primarily metabolized by CYP3A4.

Excretion

In healthy adult subjects, the mean % of total radioactivity excreted in feces was 77.3% (4.2% to 9.1% unchanged) and 88.5% (7.8% to 24.8% unchanged), and in urine was 15.5% (9.6% to 14.1% unchanged) and 5.3% (unchanged not determined) following 150 mg IV or 600 mg oral XENLETA, respectively.

Specific Populations

No clinically significant differences in the pharmacokinetics of XENLETA were observed based on age, sex, race, weight, or renal impairment including patients receiving hemodialysis.

Patients with Hepatic Impairment

The disposition of lefamulin was evaluated in non-infected subjects with normal hepatic function and with moderate (Child-Pugh Class B) or severe (Child-Pugh Class C) hepatic impairment following administration of XENLETA Injection. The half-life of lefamulin is prolonged in subjects with severe hepatic impairment compared to that in subjects with normal hepatic function (17.5 h versus 11.5 h). Protein binding of lefamulin is reduced in subjects with hepatic impairment. Therefore, unbound (biologically active) lefamulin concentrations increased with the degree of hepatic impairment. On average, unbound lefamulin plasma AUC0-inf was increased 3-fold in subjects with severe hepatic impairment compared to that in subjects with normal hepatic function. There is no information to evaluate the effect of hepatic impairment on the disposition of lefamulin following administration of XENLETA Tablets. Thus, XENLETA Tablets are not recommended in patients with moderate or severe hepatic impairment [see Dosage and Administration (2.2) and Use in Specific Populations (8.6)].

Drug Interaction Studies

Clinical Studies

Effect of Other Drugs on the Pharmacokinetics of Lefamulin

Strong CYP3A inducers or P-gp inducers: oral rifampin (strong inducer) reduced the mean lefamulin AUC0-inf and Cmax by 28% and 8%, respectively, when administered concomitantly with XENLETA Injection. Additionally, oral rifampin reduced the mean lefamulin AUC0-inf and Cmax by 72% and 57%, respectively, when administered concomitantly with XENLETA Tablets.

Strong CYP3A inhibitors or P-gp inhibitors: oral ketoconazole (strong inhibitor) increased the mean lefamulin AUC0-inf and Cmax by 31% and 6%, respectively, when administered concomitantly with XENLETA Injection. Additionally, oral ketoconazole (strong inhibitor) increased the lefamulin AUC0-inf and Cmax by 165% and 58%, respectively, when administered concomitantly with XENLETA tablets.

Effect of Lefamulin on the Pharmacokinetics of Other Drugs

CYP3A Substrates: No clinically significant differences in the pharmacokinetics of midazolam were observed when administered concomitantly with XENLETA Injection. Mean AUC0-inf and Cmax of midazolam were increased by approximately 200% and 100%, respectively, when oral midazolam (CYP3A substrate) was administered concomitantly with and at 2 or 4 hours after administration of XENLETA Tablets.

P-gp substrates: No clinically significant differences in the pharmacokinetics of digoxin (P-gp substrate) were observed when administered concomitantly with XENLETA Tablets.

In Vitro Studies Where Drug Interaction Potential Was Not Further Evaluated Clinically

Lefamulin inhibited CYP2C8 (IC50=37.0 mcg/mL), BCRP (Breast Cancer Resistance Protein) (IC50=21.4 mcg/mL), and MATE1 (IC50=0.15 mcg/mL).

12.4 Microbiology

Mechanism of Action

XENLETA is a systemic pleuromutilin antibacterial. It inhibits bacterial protein synthesis through interactions (hydrogen bonds, hydrophobic interactions, and Van der Waals forces) with the A- and P-sites of the peptidyl transferase center (PTC) in domain V of the 23s rRNA of the 50S subunit. The binding pocket of the bacterial ribosome closes around the mutilin core for an induced fit that prevents correct positioning of tRNA.

XENLETA is bactericidal in vitro against S. pneumoniae, H. influenzae and M. pneumoniae (including macrolide-resistant strains), and bacteriostatic against S. aureus and S. pyogenes at clinically relevant concentrations.

XENLETA is not active against Enterobacteriaceae and Pseudomonas aeruginosa.

Resistance

The resistance frequency to XENLETA due to spontaneous mutations in vitro at 2-8 times the MIC was 2 x 10^-9 to <2 x 10^-11 for S. aureus, <1 x 10^-9 to <3 x 10^-10 for S. pneumoniae, and <4 x 10^-9 to <2 x 10^-10 for S. pyogenes. Resistance development at sub-MIC concentrations required greater than 1 mutational step with no resistant clones detected at ≥4-times MIC.

Resistance mechanisms that affect XENLETA include specific protection or modification of the ribosomal target by ABC-F proteins such as vga (A, B, E), lsa(E), sal(A), Cfr methyl transferase, or by mutations of ribosomal proteins L3 and L4. Cfr methyl transferase has the potential to mediate cross-resistance between lefamulin and phenicols, lincosamides, oxazolidinones, and streptogramin A antibacterials.

Some isolates resistant to β-lactams, glycopeptides, macrolides, mupirocin, quinolones, tetracyclines, and trimethoprim-sulfamethoxazole may be susceptible to XENLETA.

Interaction with Other Antimicrobials

In vitro studies demonstrated no antagonism between XENLETA and other antibacterial drugs (e.g., amikacin, azithromycin, aztreonam, ceftriaxone, levofloxacin, linezolid, meropenem, penicillin, tigecycline, trimethoprim/sulfamethoxazole, and vancomycin).

XENLETA has demonstrated synergy in vitro with doxycycline against S. aureus.

Antimicrobial Activity

XENLETA has been shown to be active against most isolates of the following microorganisms, both in vitro and in clinical infections [see Indications and Usage (1.1)]:

Gram-positive Bacteria

Streptococcus pneumoniae

Staphylococcus aureus (methicillin-susceptible isolates)

Gram-negative Bacteria

Haemophilus influenzae

Other Bacteria

Mycoplasma pneumoniae

Chlamydophila pneumoniae

Legionella pneumophila

At least 90% of the following bacteria exhibit an in vitro minimum inhibitory concentration (MIC) less than or equal to the susceptible breakpoints for XENLETA against isolates of similar genus or organism group. However, the safety and efficacy of XENLETA in treating clinical infections due to these bacteria has not been established in adequate and well-controlled clinical trials.

Gram-positive Bacteria

Staphylococcus aureus (methicillin-resistant [MRSA] isolates)

Streptococcus agalactiae

Streptococcus anginosus

Streptococcus mitis

Streptococcus pyogenes

Streptococcus salivarius

Gram-negative Bacteria

Haemophilus parainfluenzae

Moraxella catarrhalis

Susceptibility Test Methods

For specific information regarding susceptibility test interpretive criteria and associated test methods and quality control standards recognized by FDA for this drug, please see: https://www.fda.gov/STIC.

13 NONCLINICAL TOXICOLOGY

13.1 Carcinogenesis, Mutagenesis, Impairment of Fertility

Long-term carcinogenicity studies have not been conducted with lefamulin.

Lefamulin did not elicit genotoxic potential in an in vivo rat bone marrow micronucleus assay for clastogenicity or in the in vitro Mouse Lymphoma Ly5178Y TK+/- mutation assay. The main human metabolite of lefamulin (2R-hydroxy lefamulin) also did not elicit genotoxic potential in the in vitro Mouse Lymphoma Ly5178Y TK+/- mutation assay.

In rats, there were no effects on male fertility that were considered to be related to lefamulin. Reproductive indices including mating behavior and fertility were not changed in any group in either gender at the highest dose tested (75 mg/kg/day, approximately 0.7 times the mean exposure of CABP patients treated IV, based on AUC0-24h); that dose was the NOAEL for fertility in male rats. In females, abnormal estrous cycling and increased post-implantation loss were observed at the high dose, making the NOAEL for fertility and early embryonic development in female rats the next highest dose, 50 mg/kg/day (approximately 0.5 times the mean exposure of CABP patients treated IV).

13.2 Animal Toxicology and/or Pharmacology

Following IV administration of lefamulin to rats for 4 or 13 weeks, anemia (all doses), increased coagulation times, and lower organ weights and histopathological changes in spleen (decreased peri-arteriolar lymphoid sheath, decreased size of the marginal zone) and thymus (cortical atrophy) were seen in rats at exposures greater than approximately 0.7 times exposure in CABP patients after IV administration in the 4-week study and greater than approximately 0.3 times exposure in CABP patients in the 13-week study.

In cynomolgus monkeys administered IV lefamulin, anemia and pancreatic microvesicular vacuolization of acinar cells were noted at exposures greater than approximately 1.6 times exposure in CABP patients in a 4-week study. In a 13-week study, pancreatic microvesicular vacuolization of acinar cells and minimal alveolar macrophage infiltrates in the lung were observed at all doses, and anemia was noted at exposures greater than approximately 1.0 times clinical exposure.

Lefamulin was evaluated in 4-week oral toxicology studies in rats and cynomolgus monkeys. Findings included partially reversible degenerative changes in the stomach and evidence of lymphoid depletion and hematopoietic cell depletion in rats at exposures greater than approximately 0.6 times exposure following oral administration to CABP patients. Findings in cynomolgus monkeys included myocardial vacuolation and fibrosis at exposures equal to or greater than 0.3 times that in CABP patients.

Evidence of dose-dependent regenerative anemia in both species may indicate that XENLETA was potentially hemolytic at a concentration that is approximately ten times higher than the concentration of the infusion solution which will be used clinically. This effect was not apparent from an in vitro evaluation of blood compatibility using human blood at a concentration of 0.6 mg/mL.

14 CLINICAL STUDIES

14.1 Community-Acquired Bacterial Pneumonia

A total of 1289 adults with CABP were randomized in two multicenter, multinational, double-blind, double-dummy, non-inferiority trials (Trial 1 NCT #02559310 and Trial 2 NCT #02813694). Trial 1 compared 5 to 10 days of XENLETA to 7 to 10 days of moxifloxacin ± linezolid. Trial 2 compared 5 days of XENLETA to 7 days of moxifloxacin.

In Trial 1, 276 patients were randomized to XENLETA (150 mg by intravenous [IV] infusion over 60 minutes every 12 hours, with the option to switch to 600 mg orally every 12 hours after at least 3 days of IV treatment) and 275 patients were randomized to moxifloxacin (400 mg IV every 24 hours, with the option to switch to 400 mg orally every 24 hours after at least 3 days of IV treatment). If methicillin-resistant Staphylococcus aureus (MRSA) was suspected at screening, patients randomized to moxifloxacin were to receive adjunctive linezolid (600 mg IV every 12 hours, with the option to switch to 600 mg orally every 12 hours after at least 3 days of IV treatment), and patients randomized to XENLETA were to receive linezolid placebo. Patients were predominantly male (60%) and white (87%). Approximately 72% of patients were PORT Risk Class III and 28% were PORT Risk Class IV or V. Median age was 62 (range 19-91) years, approximately 18% of patients were 75 years or older, and median body mass index (BMI) was 25.8 (range 11-58.4) kg/m^2. Approximately 53% of patients had creatinine clearance (CrCl) <90 mL/min. Common comorbid conditions included hypertension (41%), asthma/chronic obstructive pulmonary disease (COPD) (17%), and diabetes mellitus (13%).

In Trial 2, 370 patients were randomized to XENLETA (600 mg orally every 12 hours for 5 days) and 368 patients were randomized to moxifloxacin (400 mg orally every 24 hours for 7 days). Patients were predominantly male (52%) and white (74%). Approximately 50% of patients were PORT Risk Class II and 49% were PORT Risk Class III or IV. Median age was 59 (range 19-97) years, approximately 16% of patients were 75 years or older, and median BMI was 26.0 (range 13-63.9) kg/m^2. Approximately 50% of patients had CrCl <90 mL/min. Common comorbid conditions included hypertension (36%), asthma/COPD (16%), and diabetes mellitus (13%).

In both trials, efficacy was determined by Early Clinical Response (ECR) at 72 to 120 hours after the first dose in the Intent-to-treat (ITT) Analysis Set, which comprised all randomized patients. Patients entered the trials with at least three of four symptoms consistent with CABP (cough, sputum production, chest pain, and/or dyspnea). Response was defined as survival with improvement of at least two symptoms, no worsening of any symptom, and no receipt of non-study antibacterial treatment for CABP. Table 5 summarizes ECR rates in the two trials.

Table 5: Early Clinical Response Rates in Trial 1 and Trial 2 (ITT Analysis Set)
Study | XENLETA n/N (%) | Moxifloxacin n/N (%)* | Treatment Difference (95% CI)**
Trial 1 | 241/276 (87.3) | 248/275 (90.2) | -2.9 (-8.5, 2.8)
Trial 2 | 336/370 (90.8) | 334/368 (90.8) | 0.1 (-4.4, 4.5)
*Trial 1 compared XENLETA to moxifloxacin ± linezolid.
**95% confidence interval for the treatment difference.

Clinical response was also assessed by the Investigator at the Test of Cure (TOC) Visit 5 to 10 days after the last dose of study drug. Response was defined as survival with improvement of signs and symptoms based on the Investigator’s assessment and no receipt of non-study antibacterial treatment for CABP. Table 6 summarizes Investigator-assessed Clinical Response (IACR) rates at TOC in the ITT Analysis Set, which comprised all randomized patients.

Table 6: Investigator-assessed Clinical Response Rates at TOC in Trial 1 and Trial 2 (ITT Analysis Set)
Study | XENLETA n/N (%) | Moxifloxacin n/N (%)* | Treatment Difference (95% CI)**
Trial 1 | 223/276 (80.8) | 230/275 (83.6) | -2.8 (-9.6, 3.9)
Trial 2 | 322/370 (87.0) | 328/368 (89.1) | -2.1 (-7.0, 2.8)
*Trial 1 compared XENLETA to moxifloxacin ± linezolid.
**95% confidence interval for the treatment difference.

Table 7 summarizes IACR rates at TOC by the most common baseline pathogens across both trials in the microITT Analysis Set, which comprised all randomized patients with at least 1 baseline pathogen.

Table 7: Investigator-assessed Clinical Response Rates at TOC by Baseline Pathogen in Trial 1 and Trial 2 (microITT Analysis Set)
Pathogen | XENLETA n/N (%) | Moxifloxacin n/N (%)*
Streptococcus pneumoniae | 184/216 (85.2) | 193/223 (86.5)
Methicillin-susceptible Staphylococcus aureus (MSSA) | 14/16 (87.5) | 5/5 (100.0)
Haemophilus influenzae | 95/107 (88.8) | 88/105 (83.8)
Mycoplasma pneumoniae | 35/39 (89.7) | 33/34 (97.1)
Legionella pneumophila | 27/34 (79.4) | 26/31 (83.9)
Chlamydophila pneumoniae | 20/27 (74.1) | 23/31 (74.2)
*Trial 1 compared XENLETA to moxifloxacin ± linezolid.

16 HOW SUPPLIED/STORAGE AND HANDLING

XENLETA is supplied in the following strengths and package configurations:

XENLETA Injection

How Supplied

XENLETA Injection is a clear, colorless, sterile, nonpyrogenic solution for intravenous administration containing 150 mg of lefamulin in 15 mL 0.9% sodium chloride in a single-dose vial intended for dilution in 250 mL of 10 mM citrate buffered (pH 5) 0.9% sodium chloride. The drug product is provided in a clear type I glass 15 mL vial with a gray rubber stopper, aluminum seal and flip off cap. The diluent is provided in infusion bags containing 250 mL of sterile, nonpyrogenic 10 mM citrate buffered (pH 5) 0.9% sodium chloride solution. The vial stopper and infusion bag are not made with natural rubber latex.

They are supplied as follows:

150 mg single dose lefamulin vials (NDC 72000-120-06); packed in cartons of 6.

250 mL citrate buffer diluent bags (NDC 72000-030-06); packed in cartons of 6.

Storage and Handling

XENLETA Injection should be stored at 2°C to 8°C (36°F to 46°F). Store in a refrigerator. Do not freeze. The diluent bags should be stored in barrier overwrap at 2°C to 25°C (36°F to 77°F) until ready to use. [see Dosage and Administration (2.5)].

XENLETA Tablets

How Supplied

XENLETA Tablets are available as blue, oval, film-coated tablets containing 600 mg lefamulin. The tablets are printed with ‘LEF 600’ in black on one side.

They are supplied as follows:

Child-resistant blister cards of 10 tablets (NDC 72000-110-10).

HDPE bottles of 30 tablets with Child-resistant Closure (NDC 72000-110-30).

Storage and Handling

XENLETA Tablets should be stored at 20°C to 25°C (68°F to 77°F); excursions permitted to 15°C to 30°C (59°F to 86°F) [see USP Controlled Room Temperature].

17 PATIENT COUNSELING INFORMATION

Diarrhea

Advise patients that diarrhea is a common problem caused by antibacterial drugs, including XENLETA, which usually ends when the antibacterial drug is discontinued. Sometimes after starting treatment with an antibacterial drug, patients can develop watery stools (with or without stomach cramps and fever) which may be a sign of a more serious intestinal infection, even as late as 2 or more months after having taken the last dose of the antibacterial drug. If this occurs, instruct patients to contact their healthcare provider as soon as possible [see Warnings and Precautions (5.3), and Adverse Reactions (6.1)].

Nausea and Vomiting

Advise patients that nausea and vomiting are common adverse reactions to XENLETA [see Adverse Reactions (6.1)].

Drug Interactions

Advise patients of the potential interaction other medications can have with XENLETA or the effect XENLETA may have on other medications, as these interactions may result in decreased effectiveness or increased toxicities of either XENLETA or the other medications. Patients should alert their physician if they are currently taking any medication(s) (including herbal or nutritional supplements) or are prescribed new medication(s) during treatment with XENLETA [see Drug Interactions (7)].

Allergic Reactions

Advise patients that allergic reactions, including serious allergic reactions, could occur with XENLETA and that serious allergic reactions require immediate treatment. Ask the patient about any previous hypersensitivity reactions to XENLETA, or other pleuromutilin class antibacterial drugs [see Contraindications (4)].

Administration with Food

Advise patients that XENLETA should be taken at least 1 hour before a meal or 2 hours after a meal and should be swallowed whole with water (6 to 8 ounces). XENLETA should not be crushed or divided [see Dosage and Administration (2.3) and Clinical Pharmacology (12.3)].

Embryo-Fetal Toxicity

Advise pregnant women and females of reproductive potential of the potential risk to a fetus, and to inform their healthcare provider of a known or suspected pregnancy. Advise patients to avoid becoming pregnant while receiving this drug [see Warnings and Precautions (5.2) and Use in Specific Populations (8.1)].

Advise females of reproductive potential to use effective contraception during treatment with XENLETA and for 2 days after the final dose [see Warnings and Precautions (5.2) and Use in Specific Populations (8.3)].

Inform patients that Nabriva Therapeutics has a surveillance program for pregnant women who have inadvertently taken XENLETA during pregnancy. Advise patients to call 1-855-5NABRIVA to enroll [see Use in Specific Populations (8.1)].

Lactation

Advise lactating women to pump and discard human milk for the duration of treatment with XENLETA and for 2 days after the final dose [see Use in Specific Populations (8.2)].

Antibacterial Resistance

Patients should be counseled that antibacterial drugs including XENLETA should only be used to treat bacterial infections. They do not treat viral infections (e.g., the common cold). When XENLETA is prescribed to treat a bacterial infection, patients should be told that although it is common to feel better early in the course of treatment, the medication should be taken exactly as directed. Skipping doses or not completing the full course of therapy may (1) decrease the effectiveness of the immediate treatment and (2) increase the likelihood that bacteria will develop resistance and will not be treatable by XENLETA or other antibacterial drugs in the future [see Warnings and Precautions (5.4)].

Distributed by:

Nabriva Therapeutics US, Inc.

Fort Washington, PA 19034

Nabriva Therapeutics is a trademark of Nabriva Therapeutics US, Inc.

XENLETA is a trademark of Nabriva Therapeutics US, Inc.

For patent information: www.nabriva.com/patents

Copyright © 2019-2021 Nabriva Therapeutics US, Inc., an affiliate of Nabriva Therapeutics Ireland DAC. All rights reserved.